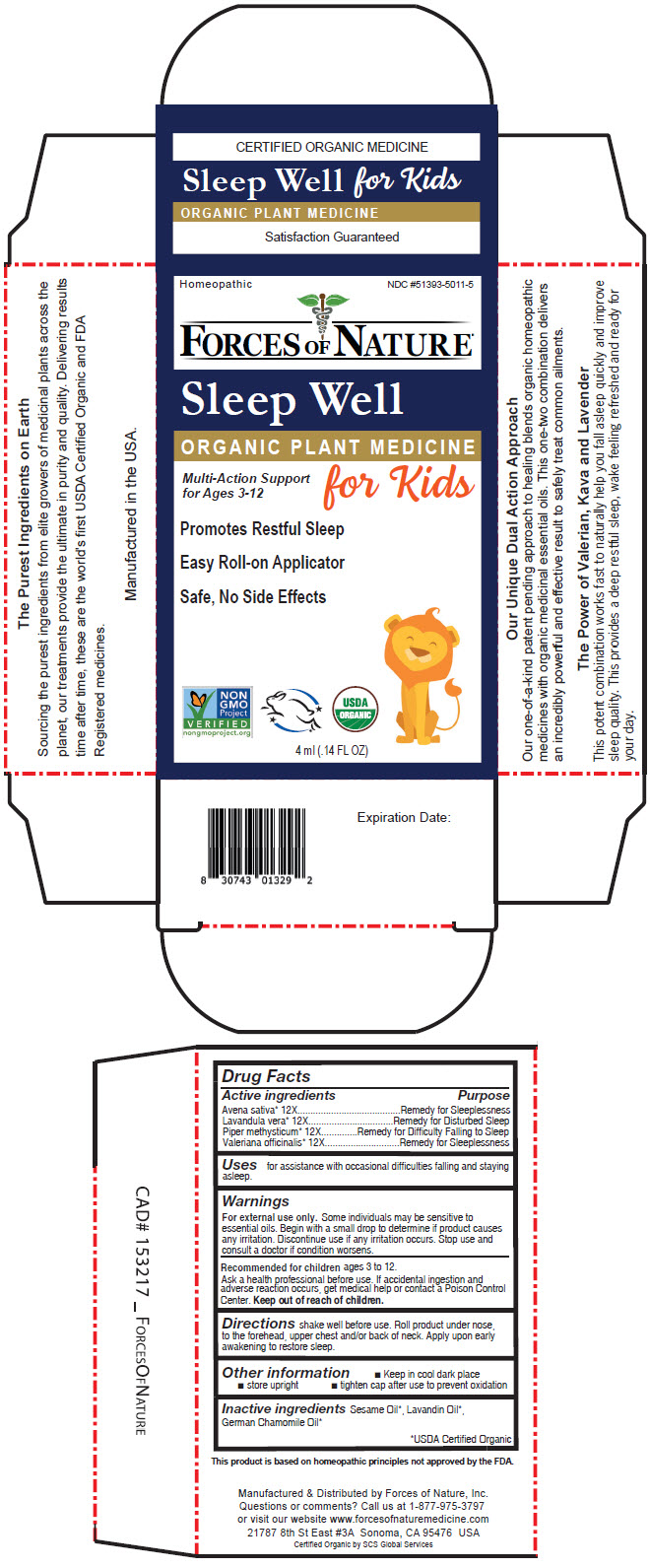 DRUG LABEL: Sleep Kids
NDC: 51393-5010 | Form: SOLUTION/ DROPS
Manufacturer: Forces of Nature
Category: homeopathic | Type: HUMAN OTC DRUG LABEL
Date: 20220930

ACTIVE INGREDIENTS: Avena Sativa Top 12 [hp_X]/100 mL; Lavandula Angustifolia Subsp. Pyrenaica Whole 12 [hp_X]/100 mL; Macropiper Methysticum Root 12 [hp_X]/100 mL; Valerian 12 [hp_X]/100 mL
INACTIVE INGREDIENTS: Sesame Oil; Lavandin Oil; Chamomile Flower Oil

Sleep Kids

Drug Facts

ACTIVE INGREDIENT

Active ingredients | Purpose
Avena sativa [USDA Certified Organic] 12X | Remedy for Sleeplessness
Lavandula vera 12X | Remedy for Disturbed Sleep
Piper methysticum 12X | Remedy for Difficulty Falling to Sleep
Valeriana officinalis 12X | Remedy for Sleeplessness

Uses

for assistance with occasional difficulties falling and staying asleep.

Warnings

For external use only. Some individuals may be sensitive to essential oils. Begin with a small drop to determine if product causes any irritation. Discontinue use if any irritation occurs. Stop use and consult a doctor if condition worsens.

Recommended for children ages 3 to 12.

KEEP OUT OF REACH OF CHILDREN

Ask a health professional before use. If accidental ingestion and adverse reaction occurs, get medical help or contact a Poison Control Center. Keep out of reach of children.

Directions

shake well before use. Roll product under nose, to the forehead, upper chest and/or back of neck. Apply upon early awakening to restore sleep.

Other information

- Keep in cool dark place
- store upright
- tighten cap after use to prevent oxidation

Inactive ingredients

Sesame Oil, Lavandin Oil, German Chamomile Oil

Questions or comments?

Call us at 1-877-975-3797 or visit our website www.forcesofnaturemedicine.com

Manufactured & Distributed by Forces of Nature, Inc.
21787 8th St East #3A Sonoma, CA 95476 USA

PRINCIPAL DISPLAY PANEL - 4 ml Bottle Carton

Homeopathic
NDC #51393-5011-5

FORCES OF NATURE®

Sleep Well

ORGANIC PLANT MEDICINE

Multi-Action Support
for Ages 3-12

for Kids

Promotes Restful Sleep

Easy Roll-on Applicator

Safe, No Side Effects

NON
GMO
Project
VERIFIED
nongmoproject.org

USDA
ORGANIC

4 ml (.14 FL OZ)